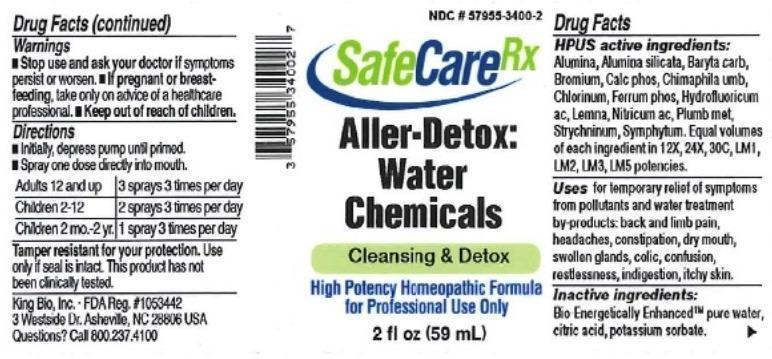 DRUG LABEL: Aller Detox Water Chemicals
NDC: 57955-3400 | Form: LIQUID
Manufacturer: King Bio Inc.
Category: homeopathic | Type: HUMAN OTC DRUG LABEL
Date: 20150819

ACTIVE INGREDIENTS: ALUMINUM OXIDE 12 [hp_X]/59 mL; KAOLIN 12 [hp_X]/59 mL; BARIUM CARBONATE 12 [hp_X]/59 mL; BROMINE 12 [hp_X]/59 mL; TRIBASIC CALCIUM PHOSPHATE 12 [hp_X]/59 mL; CHIMAPHILA UMBELLATA 12 [hp_X]/59 mL; CHLORINE 12 [hp_X]/59 mL; FERROSOFERRIC PHOSPHATE 12 [hp_X]/59 mL; HYDROFLUORIC ACID 12 [hp_X]/59 mL; LEMNA MINOR 12 [hp_X]/59 mL; NITRIC ACID 12 [hp_X]/59 mL; LEAD 12 [hp_X]/59 mL; STRYCHNINE 12 [hp_X]/59 mL; COMFREY ROOT 12 [hp_X]/59 mL
INACTIVE INGREDIENTS: WATER; ANHYDROUS CITRIC ACID; POTASSIUM SORBATE

Aller Detox Water Chemicals

ACTIVE INGREDIENT

Drug Facts__________________________________________________________________________________________________________

HPUS active ingredients: Alumina, Alumina silicata, Baryta carbonica, Bromium, Calcarea phosphorica, Chimaphila umbellata, Chlorinum, Ferrum phosphoricum, Hydrofluoricum acidum, Lemna minor, Nitricum acidum, Plumbum metallicum, Strychninum, Symphytum officinale. Equal volumes of each ingredient in 12X, 24X, 30C, LM1, LM2, LM3, LM5 potencies.

INDICATIONS AND USAGE

Uses for temporary relief of symptoms from pollutants and water treatment by-products: back and limb pain, headaches, constipation, dry mouth, swollen glands, colic, confusion, restlessness, indigestion, itchy skin.

Inactive Ingredients:

Bio-Energetically Enhanced™ pure water, citric acid and potassium sorbate.

Warnings

- Stop use and ask your doctor if symptoms persist or worsen.
- If pregnant or breast-feeding, take only on advice of a healthcare professional.

- Keep out of reach of children.

Directions

- Initially, depress pump until primed.
- Spray one dose directly into mouth.
- Adults 12 and up: 3 sprays 3 times per day
- Children 2-12: 2 sprays 3 times per day.
- Children 2mo.-2 yr: 1 spray 3 times per day.

OTHER SAFETY INFORMATION

Tamper resistant for your protection. Use only if safety seal is intact.

PURPOSE

Uses for temporary relief of symptoms from pollutants and water treatment by-products:

- back and limb pain
- headaches
- constipation
- dry mouth
- swollen glands
- colic
- confusion
- restlessness
- indigestion
- itchy skin